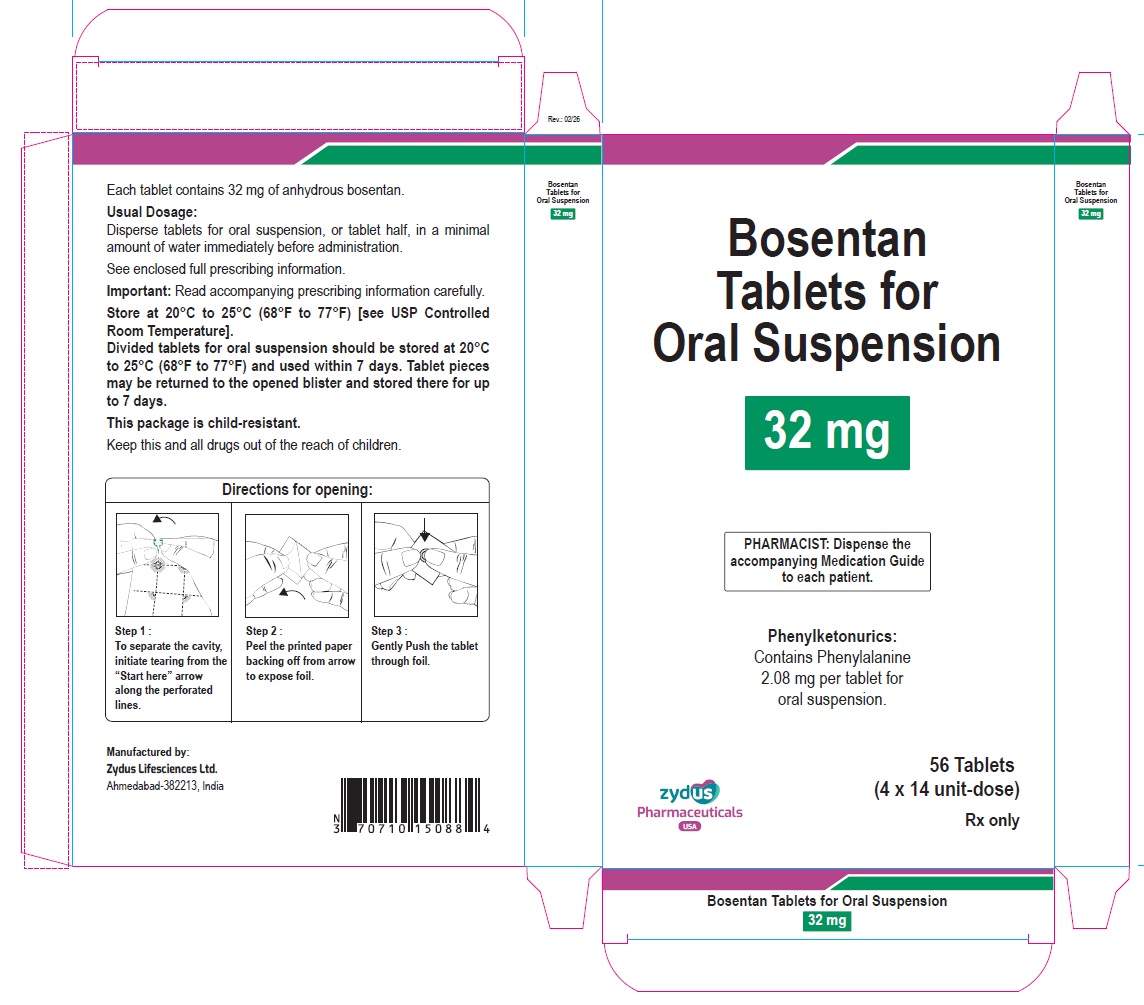 DRUG LABEL: bosentan
NDC: 70771-1908 | Form: TABLET, FOR SUSPENSION
Manufacturer: Zydus Lifesciences Limited
Category: prescription | Type: HUMAN PRESCRIPTION DRUG LABEL
Date: 20260214

ACTIVE INGREDIENTS: BOSENTAN 32 mg/1 1
INACTIVE INGREDIENTS: ACESULFAME POTASSIUM; ASPARTAME; CROSCARMELLOSE SODIUM; DIMETHYLAMINOETHYL METHACRYLATE - BUTYL METHACRYLATE - METHYL METHACRYLATE COPOLYMER; MAGNESIUM STEARATE; MANNITOL; SILICON DIOXIDE; SODIUM LAURYL SULFATE; STARCH, CORN; STEARIC ACID; TALC

Bosentan Tablets for Oral Suspension

PACKAGE LABEL.PRINCIPAL DISPLAY PANEL

NDC 70771-1908-8

Bosentan Tablets for Oral Suspension, 32 mg

PHARMACIST: Dispense the accompanying Medication Guide to each patient.

Phenylketonurics: Contains Phenylalanine 2.08 mg per tablet for oral suspension.

56 Tablets (4 x 14 unit-dose)

Rx only

Zydus